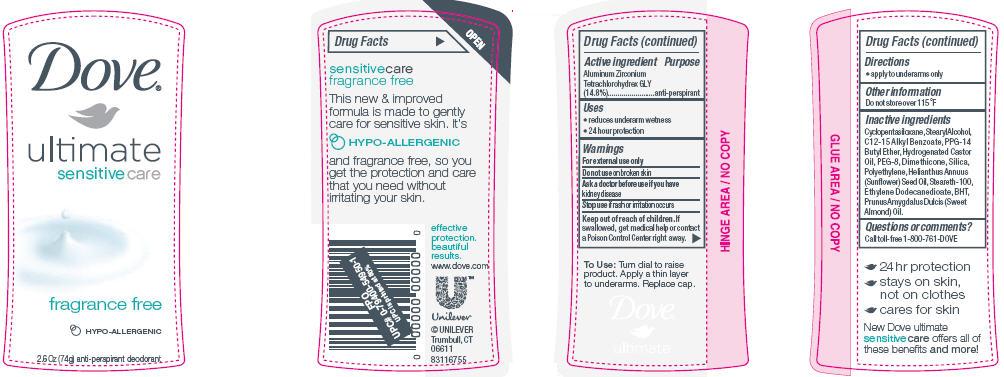 DRUG LABEL: Dove Ultimate Sensitive Care Fragrance Free
NDC: 64942-1090 | Form: STICK
Manufacturer: Conopco Inc. d/b/a Unilever
Category: otc | Type: HUMAN OTC DRUG LABEL
Date: 20100325

ACTIVE INGREDIENTS: Aluminum Zirconium Tetrachlorohydrex GLY 14.8 g/100 g

Dove Ultimate Sensitive Care Fragrance Free Antiperspirant and Deodorant

Active ingredient Purpose

Aluminum Zirconium Tetrachlorohydrex GLY (14.8%).......................................antiperspirant

WARNINGS

For external use only

Do not use on broken skin

Ask a doctor before use if you have kidney disease

Stop use if rash or irritation occurs

Keep out of reach of children. If swallowed, get medical help or contact a Poison Control Center right away.

Inactive Ingredients
Cyclopentasiloxane, Stearyl Alcohol, C12-15 Alkyl Benzoate, PPG-14 Butyl Ether, Hydrogenated Castor Oil, PEG-8, Dimethicone, Silica, Polyethylene, Helianthus Annuus (Sunflower) Seed Oil, Steareth-100, Ethylene Dodecanedioate, BHT, Prunus Amygdalus Dulcis (Sweet Almond) Oil.

Questions or comments?

Call toll-free 1-800-761-DOVE

PACKAGE LABEL

PDP 2.6 oz